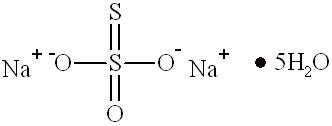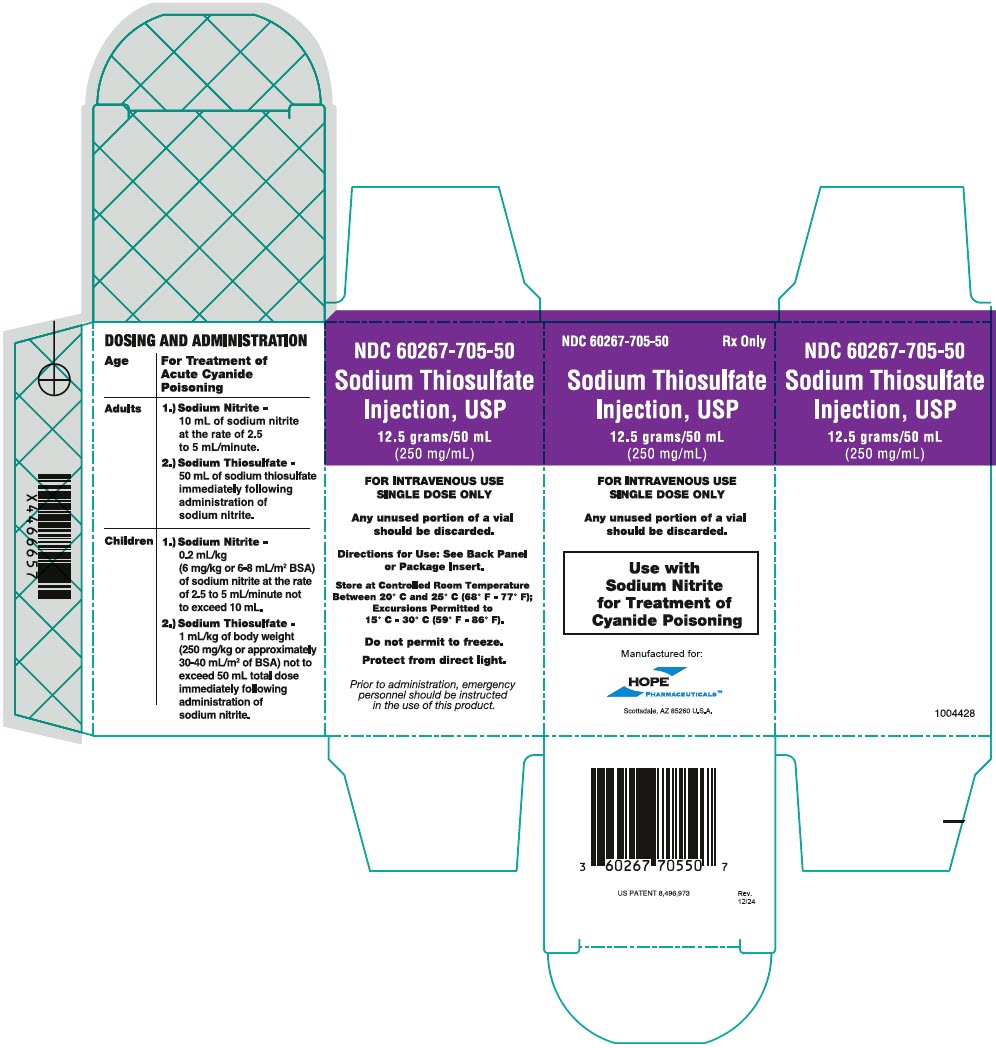 DRUG LABEL: Sodium Thiosulfate
NDC: 60267-705 | Form: INJECTION, SOLUTION
Manufacturer: Hope Pharmaceuticals
Category: prescription | Type: HUMAN PRESCRIPTION DRUG LABEL
Date: 20251006

ACTIVE INGREDIENTS: Sodium Thiosulfate 250 mg/1 mL
INACTIVE INGREDIENTS: Potassium Chloride 4.4 mg/1 mL; Boric Acid 2.8 mg/1 mL; Water; Sodium Hydroxide; Nitrogen

HIGHLIGHTS OF PRESCRIBING INFORMATION

These highlights do not include all the information needed to use the SODIUM THIOSULFATE INJECTION safely and effectively. See full prescribing information for SODIUM THIOSULFATE INJECTION.
Sodium Thiosulfate Injection, USP
Initial U.S. Approval: 1992

1 INDICATIONS AND USAGE

Sodium Thiosulfate Injection, an antidote, is indicated for sequential use with sodium nitrite for treatment of acute cyanide poisoning that is judged to be serious or life-threatening. (1)

- Use with caution if the diagnosis of cyanide poisoning is uncertain. (1)

2. DOSAGE AND ADMINISTRATION

- If clinical suspicion of cyanide poisoning is high, administer Sodium Thiosulfate Injection without delay and in conjunction with appropriate airway, ventilatory, and circulatory support. (2.1)
- The expert advice of a regional poison control center may be obtained by calling 1-800-222-1222. (2.1)

Dosing:

Age | Intravenous Dose of Sodium Nitrite and Sodium Thiosulfate
Adults | 1.) Sodium Nitrite -10 mL of sodium nitrite at the rate of 2.5 to 5 mL/minute 2.) Sodium Thiosulfate - 50 mL of sodium thiosulfate immediately following administration of sodium nitrite.
Children | 1.) Sodium Nitrite - 0.2 mL/kg (6 mg/kg or 6-8 mL/m^2 BSA) of sodium nitrite at the rate of 2.5 to 5 mL/minute not to exceed 10 mL 2.) Sodium Thiosulfate - 1 mL/kg of body weight (250 mg/kg or approximately 30-40 mL/m^2 of BSA) not to exceed 50 mL total dose immediately following administration of sodium nitrite.

- Redosing: If signs of cyanide poisoning reappear, repeat treatment using one-half the original dose of both sodium nitrite and sodium thiosulfate. (2.2)
- Monitoring: Blood pressure must be monitored during treatment. (2.2)
- Sodium thiosulfate is chemically incompatible with hydroxocobalamin and should not be administered via the same intravenous line. (2.4)

3 DOSAGE FORMS AND STRENGTHS

Sodium Thiosulfate Injection consists of:

- One vial of sodium thiosulfate injection USP 12.5 grams/50 mL (250 mg/mL) (3)

4 CONTRAINDICATIONS

- None. (4)

5 WARNINGS AND PRECAUTIONS

- Sulfites: Sodium thiosulfate may contain trace impurities of sodium sulfite (5.1)

6 ADVERSE REACTIONS

Most common adverse reactions are:

- Hypotension, headache, disorientation (6)

To report SUSPECTED ADVERSE REACTIONS, contact Hope Pharmaceuticals at 1-800-755-9595 or FDA at 1-800-FDA-1088 or www.fda.gov/medwatch.

8 USE IN SPECIFIC POPULATIONS

- Lactation: Breastfeeding not recommended. (8.2)
- Renal impairment: Sodium thiosulfate is substantially excreted by the kidney. The risk of toxic reactions to this drug may be greater in patients with impaired renal function. (8.6).

FULL PRESCRIBING INFORMATION

1 INDICATIONS AND USAGE

Sodium Thiosulfate Injection is indicated for sequential use with sodium nitrite for the treatment of acute cyanide poisoning that is judged to be serious or life-threatening. When the diagnosis of cyanide poisoning is uncertain, the potential risks associated with Sodium Thiosulfate Injection should be carefully weighed against the potential benefits, especially if the patient is not in extremis.

2. DOSAGE AND ADMINISTRATION

2.1 Important Dosage and Administration Instructions

- If clinical suspicion of cyanide poisoning is high, administer Sodium Thiosulfate Injection without delay.
- Comprehensive treatment of acute cyanide intoxication requires support of vital functions. Administration of sodium nitrite and sodium thiosulfate should be considered adjunctive to appropriate supportive therapies. Airway, ventilatory and circulatory support, and oxygen administration should not be delayed in order to administer sodium nitrite and sodium thiosulfate [see Warnings and Precautions (5.1)].
- The expert advice of a regional poison control center may be obtained by calling 1-800-222-1222.

Identifying Patients with Cyanide Poisoning

Cyanide poisoning may result from inhalation, ingestion, or dermal exposure to various cyanide-containing compounds, including smoke from closed-space fires. Sources of cyanide poisoning include hydrogen cyanide and its salts, cyanogenic plants, aliphatic nitriles, and prolonged exposure to sodium nitroprusside.

The presence and extent of cyanide poisoning are often initially unknown. There is no widely available, rapid, confirmatory cyanide blood test. Treatment decisions must be made on the basis of clinical history and signs and symptoms of cyanide intoxication.

Table 1. Common Signs and Symptoms of Cyanide Poisoning
Symptoms | Signs
- Headache - Confusion - Dyspnea - Chest Tightness - Nausea | - Altered Mental Status (e.g., confusion, disorientation) - Seizures or Coma - Mydriasis - Tachypnea/Hyperpnea (early) - Bradypnea/Apnea (late) - Hypertension (early)/ Hypotension (late) - Cardiovascular Collapse - Vomiting - Plasma Lactate Concentration ≥ 8 mmol/L

In some settings, panic symptoms including tachypnea and vomiting may mimic early cyanide poisoning signs. The presence of altered mental status (e.g., confusion and disorientation) and/or mydriasis is suggestive of true cyanide poisoning although these signs can occur with other toxic exposures as well.

Smoke Inhalation

Not all smoke inhalation victims will have cyanide poisoning and may present with burns, trauma, and exposure to other toxic substances making a diagnosis of cyanide poisoning particularly difficult. Prior to administration of Sodium Thiosulfate Injection, smoke-inhalation victims should be assessed for the following:

- Exposure to fire or smoke in an enclosed area
- Presence of soot around the mouth, nose, or oropharynx
- Altered mental status

Although hypotension is highly suggestive of cyanide poisoning, it is only present in a small percentage of cyanide-poisoned smoke inhalation victims. Also indicative of cyanide poisoning is a plasma lactate concentration greater than or equal to 10 mmol/L (a value higher than that typically listed in the table of signs and symptoms of isolated cyanide poisoning because carbon monoxide associated with smoke inhalation also contributes to lactic acidemia). If cyanide poisoning is suspected, treatment should not be delayed in order to obtain a plasma lactate concentration.

Use with Other Cyanide Antidotes

The safety of administering other cyanide antidotes simultaneously with Sodium Thiosulfate Injection has not been established. If a decision is made to administer another cyanide antidote with Sodium Thiosulfate Injection, these drugs should not be administered concurrently in the same intravenous (IV) line. [see Dosage and Administration (2.2)]

2.2 Recommended Dosing

Sodium Nitrite Injection and Sodium Thiosulfate Injection are administered by slow intravenous injection. They should be given as early as possible after a diagnosis of acute life-threatening cyanide poisoning has been established. Sodium nitrite should be administered first, followed immediately by sodium thiosulfate. Blood pressure must be monitored during infusion in both adults and children. The rate of infusion should be decreased if significant hypotension is noted.

Age | Intravenous Dose of Sodium Nitrite and Sodium Thiosulfate
Adults | 1.) Sodium Nitrite -10 mL of sodium nitrite at the rate of 2.5 to 5 mL/minute 2.) Sodium Thiosulfate - 50 mL of sodium thiosulfate immediately following administration of sodium nitrite.
Children | 1.) Sodium Nitrite -0.2 mL/kg (6 mg/kg or 6-8 mL/m^2 BSA) of sodium nitrite at the rate of 2.5 to 5 mL/minute not to exceed 10 mL 2.) Sodium Thiosulfate - 1 mL/kg of body weight (250 mg/kg or approximately 30-40 mL/m^2 of BSA) not to exceed 50 mL total dose immediately following administration of sodium nitrite.

NOTE: If signs of poisoning reappear, repeat treatment using one-half the original dose of both sodium nitrite and sodium thiosulfate.

In adult and pediatric patients with known anemia, it is recommended that the dosage of sodium nitrite should be reduced proportionately to the hemoglobin concentration.

Visually inspect all parenteral drug products for particulate matter and discoloration prior to administration.

2.3 Recommended Monitoring

Patients should be monitored for at least 24-48 hours after Sodium Thiosulfate Injection administration for adequacy of oxygenation and perfusion and for recurrent signs and symptoms of cyanide toxicity. When possible, obtain hemoglobin/hematocrit when treatment is initiated. Measurements of oxygen saturation using standard pulse oximetry and calculated oxygen saturation values based on measured PO2 are unreliable in the presence of methemoglobinemia.

2.4 Incompatibility Information

Chemical incompatibility has been reported between Sodium Thiosulfate Injection and hydroxocobalamin and these drugs should not be administered simultaneously through the same IV line. No chemical incompatibility has been reported between sodium thiosulfate and sodium nitrite, when administered sequentially through the same IV line as described in Dosage and Administration.

Simultaneous administration of Sodium Thiosulfate Injection and blood products (whole blood, packed red cells, platelet concentrate and/or fresh frozen plasma) through the same intravenous line is not recommended. However, blood products and Sodium Thiosulfate Injection can be administered simultaneously using separate intravenous lines (preferably on contralateral extremities, if peripheral lines are being used).

3 DOSAGE FORMS AND STRENGTHS

Sodium Thiosulfate Injection consists of:

- One vial of sodium thiosulfate injection USP 12.5 grams/50 mL (250 mg/mL)

Administration of one vial constitutes a single dose.

4 CONTRAINDICATIONS

None

5 WARNINGS AND PRECAUTIONS

5.1 Sulfites

Sodium thiosulfate drug product may contain trace impurities of sodium sulfite. The presence of a trace amount of sulfites in this product should not deter administration of the drug for treatment of emergency situations, even if the patient is sulfite-sensitive.

6 ADVERSE REACTIONS

There have been no controlled clinical trials conducted to systematically assess the adverse events profile of sodium thiosulfate.

The medical literature has reported the following adverse events in association with sodium thiosulfate administration. These adverse events were not reported in the context of controlled trials or with consistent monitoring and reporting methodologies for adverse events. Therefore, frequency of occurrence of these adverse events cannot be assessed.

Cardiovascular system: hypotension

Central nervous system: headache, disorientation

Gastrointestinal system: nausea, vomiting

Hematological: prolonged bleeding time

Body as a Whole: salty taste in mouth, warm sensation over body

In humans, rapid administration of concentrated solutions or solutions not freshly prepared, and administration of large doses of sodium thiosulfate have been associated with a higher incidence of nausea and vomiting. However, administration of 0.1 g sodium thiosulfate per pound up to a maximum of 15 g in a 10-15% solution over 10-15 minutes was associated with nausea and vomiting in 7 of 26 patients without concomitant cyanide intoxication.

In a series of 11 human subjects, a single intravenous infusion of 50 mL of 50% sodium thiosulfate was associated with increases in clotting time 1-3 days after administration. However, no significant changes were observed in other hematological parameters.

7 DRUG INTERACTIONS

Formal drug interaction studies have not been conducted with Sodium Thiosulfate Injection.

8 USE IN SPECIFIC POPULATIONS

8.1 Pregnancy

Risk Summary

There are no available data on Sodium Thiosulfate Injection use in pregnant women to establish a drug-associated risk for major birth defects, miscarriage, or adverse maternal or fetal outcomes. There are risks to the pregnant woman and fetus associated with untreated cyanide poisoning (see Clinical Considerations). Therefore, if a pregnant woman has known or suspected cyanide poisoning, Sodium Thiosulfate Injection for sequential use with sodium nitrite is recommended [see Indications and Usage (1)]. In published animal studies, no evidence of embryotoxicity or malformations was reported when sodium thiosulfate was administered during organogenesis to pregnant mice, rats, hamsters, or rats at 0.2 to 0.9 times the human daily dose of 12.5 g for cyanide poisoning. The studies did not test doses that were comparable to the human dose for cyanide poisoning (see Data).

The estimated background risk of major birth defects and miscarriage for the indicated population is unknown. All pregnancies have a background risk of birth defect, loss, or other adverse outcomes. In the US general population, the estimated background risk of major birth defects and miscarriage in clinically recognized pregnancies is 2 to 4% and 15 to 20%, respectively.

Clinical Considerations

Disease-associated maternal and/or embryo/fetal risk

Cyanide readily crosses the placenta. Cyanide poisoning is a medical emergency in pregnancy, which can be fatal for the pregnant woman and fetus if left untreated. Life-sustaining therapy should not be withheld due to pregnancy.

Data

Animal Data:

No malformations or evidence of embryo-fetal toxicity were noted when pregnant mice, rats, hamsters, or rabbits were administered oral doses of sodium thiosulfate of up to 550, 400, 400, or 580 mg/kg, respectively during organogenesis (0.2, 0.3, 0.26, and 0.9 times the human dose of 12.5 g/60 kg person for cyanide poisoning based on body surface area).

Published studies suggest that treatment with sodium thiosulfate ameliorates the teratogenic effects of maternal cyanide poisoning in hamsters.

8.2 Lactation

Risk Summary

There are no data on the presence of sodium thiosulfate in human or animal milk, the effects on the breastfed infant, or the effects on milk production. Cyanide and thiocyanate (which is formed when sodium thiosulfate combines with cyanide) are present in human milk. Because of the potential for serious adverse reactions in the breastfed infant, breastfeeding is not recommended during treatment with Sodium Thiosulfate Injection. There are no data to determine when breastfeeding may be safely restarted following the administration of Sodium Thiosulfate Injection.

8.4 Pediatric Use

There are case reports in the medical literature of sodium nitrite in conjunction with sodium thiosulfate being administered to pediatric patients with cyanide poisoning; however, there have been no clinical studies to evaluate the safety or efficacy of sodium thiosulfate in the pediatric population. As for adult patients, dosing recommendations for pediatric patients have been based on theoretical calculations of antidote detoxifying potential, extrapolation from animal experiments, and a small number of human case reports.

8.5 Geriatric Use

Sodium thiosulfate is known to be substantially excreted by the kidney, and the risk of adverse reactions to this drug may be greater in patients with impaired renal function. Because elderly patients are more likely to have decreased renal function, care should be taken in dose selection, and it may be useful to monitor renal function.

8.6 Renal Disease

Sodium thiosulfate is known to be substantially excreted by the kidney, and the risk of toxic reactions to this drug may be greater in patients with impaired renal function. Because elderly patients are more likely to have decreased renal function, care should be taken in dose selection, and it may be useful to monitor renal function.

10 OVERDOSAGE

There is limited information about the effects of large doses of sodium thiosulfate in humans. Oral administration of 3 g sodium thiosulfate per day for 1-2 weeks in humans resulted in reductions in room air arterial oxygen saturation to as low as 75%, which was due to a rightward shift in the oxygen hemoglobin dissociation curve. The subjects returned to baseline oxygen saturations 1 week after discontinuation of sodium thiosulfate. A single intravenous administration of 20 mL of 10% sodium thiosulfate reportedly did not change oxygen saturations.

11 DESCRIPTION

Sodium thiosulfate has the chemical name thiosulfuric acid, disodium salt, pentahydrate. The chemical formula is Na2S2O3∙ 5H2O and the molecular weight is 248.17. The structural formula is:

Structure of Sodium Thiosulfate Pentahydrate

Sodium Thiosulfate Injection is a cyanide antidote which contains one 50 mL glass vial containing a 25% solution of sodium thiosulfate injection.

Sodium thiosulfate injection is a sterile aqueous solution and is intended for intravenous injection. Each vial contains 12.5 grams of sodium thiosulfate in 50 mL solution (250 mg/mL). Each mL also contains 2.8 mg boric acid and 4.4 mg of potassium chloride. The pH of the solution is adjusted with boric acid and/or sodium hydroxide. Sodium thiosulfate injection is a clear solution with a pH between 7.5 and 9.0.

12 CLINICAL PHARMACOLOGY

12.1 Mechanism of Action

Exposure to a high dose of cyanide can result in death within minutes due to the inhibition of cytochrome oxidase resulting in arrest of cellular respiration. Specifically, cyanide binds rapidly with cytochrome a3, a component of the cytochrome c oxidase complex in mitochondria. Inhibition of cytochrome a3 prevents the cell from using oxygen and forces anaerobic metabolism, resulting in lactate production, cellular hypoxia and metabolic acidosis. In massive acute cyanide poisoning, the mechanism of toxicity may involve other enzyme systems as well.

The synergy resulting from treatment of cyanide poisoning with the combination of sodium nitrite and sodium thiosulfate is the result of differences in their primary mechanisms of action as antidotes for cyanide poisoning.

Sodium Nitrite

Sodium nitrite is thought to exert its therapeutic effect by reacting with hemoglobin to form methemoglobin, an oxidized form of hemoglobin incapable of oxygen transport but with high affinity for cyanide. Cyanide preferentially binds to methemoglobin over cytochrome a3, forming the nontoxic cyanomethemoglobin. Methemoglobin displaces cyanide from cytochrome oxidase, allowing resumption of aerobic metabolism. The chemical reaction is as follows:

NaNO2 + Hemoglobin → Methemoglobin

HCN + Methemoglobin → Cyanomethemoglobin

Vasodilation has also been cited to account for at least part of the therapeutic effect of sodium nitrite. It has been suggested that sodium nitrite-induced methemoglobinemia may be more efficacious against cyanide poisoning than comparable levels of methemoglobinemia induced by other oxidants. Also, sodium nitrite appears to retain some efficacy even when the formation of methemoglobin is inhibited by methylene blue.

Sodium Thiosulfate

The primary route of endogenous cyanide detoxification is by enzymatic transulfuration to thiocyanate (SCN^-), which is relatively nontoxic and readily excreted in the urine. Sodium thiosulfate is thought to serve as a sulfur donor in the reaction catalyzed by the enzyme rhodanese, thus enhancing the endogenous detoxification of cyanide in the following chemical reaction:

Rhodanese

Na2S2O3 + CN^- → SCN^- + Na2SO3.

12. 2 Pharmacodynamics

In dogs, pretreatment with sodium thiosulfate to achieve a steady state level of 2 μmol/mL increased the rate of conversion of cyanide to thiocyanate over 30-fold.

12.3 Pharmacokinetics

Sodium Thiosulfate

Thiosulfate taken orally is not systemically absorbed. Most of the thiosulfate is oxidized to sulfate or is incorporated into endogenous sulphur compounds; a small proportion is excreted through the kidneys. Approximately 20-50% of exogenously administered thiosulfate is eliminated unchanged via the kidneys. After an intravenous injection of 1 g sodium thiosulfate in patients, the reported serum thiosulfate half-life was approximately 20 minutes. However, after an intravenous injection of a substantially higher dose of sodium thiosulfate (150 mg/kg, that is, 9 g for 60 kg body weight) in normal healthy men, the reported elimination half-life was 182 minutes.

Cyanide

The apparent terminal elimination half life and volume of distribution of cyanide, in a patient treated for an acute cyanide poisoning with sodium nitrite and sodium thiosulfate administration, have been reported to be 19 hours and 0.41 L/kg, respectively. Additionally, an initial elimination half life of cyanide has been reported to be approximately 1-3 hours.

Thiocyanate

After detoxification, in healthy subjects, thiocyanate is excreted mainly in the urine at a rate inversely proportional to creatinine clearance. In healthy subjects, the elimination half-life and volume of distribution of thiocyanate have been reported to be 2.7 days and 0.25 L/kg, respectively. However, in subjects with renal insufficiency the reported elimination half life is approximately 9 days.

13 NONCLINICAL TOXICOLOGY

13.1 Carcinogenesis, Mutagenesis, Impairment of Fertility

Carcinogenesis

Long-term studies in animals have not been performed to evaluate the potential carcinogenicity of sodium thiosulfate.

Mutagenesis:

The mutagenic potential of sodium thiosulfate has been examined in the in vitro Bacterial Reverse Mutation Assay (Ames Assay). Sodium thiosulfate was not mutagenic in the absence of metabolic activation in S. typhimurium strains TA98, TA100, TA1535, TA537, or TA1538. Sodium thiosulfate was not mutagenic in the presence of metabolic activation in strains TA 98, TA1535, TA1537, TA1538 or E. coli strain WP2.

Sodium thiosulfate was negative for clastogenic potential in the in vivo mammalian erythrocyte micronucleus assay in rats.

Impairment of Fertility:

Animal studies to examine the effects of sodium thiosulfate on fertility have not been conducted.

14 CLINICAL STUDIES

Human Data

The human data supporting the use of sodium thiosulfate for cyanide poisoning consists primarily of published case reports. There are no randomized controlled clinical trials. Nearly all the human data describing the use of sodium thiosulfate report its use in conjunction with sodium nitrite. Dosing recommendations for humans have been based on theoretical calculations of antidote detoxifying potential, extrapolation from animal experiments, and a small number of human case reports.

There have been no human studies to prospectively and systematically evaluate the safety of sodium thiosulfate or sodium nitrite in humans. Available human safety information is based largely on anecdotal case reports and case series of limited scope.

Animal Data (Cyanide Poisoning)

THE EFFECTIVENESS OF SODIUM THIOSULFATE AND SODIUM NITRITE FOR THE TREATMENT OF ACUTE CYANIDE POISONING HAS NOT BEEN STUDIED IN HUMANS IN ADEQUATE AND WELL-CONTROLLED CLINICAL TRIALS BECAUSE INDUCING THE CONDITION IN HUMANS TO STUDY THE DRUG'S EFFICACY IS NOT ETHICAL.

Due to the extreme toxicity of cyanide, experimental evaluation of treatment efficacy has predominantly been completed in animal models. The efficacy of sodium thiosulfate treatment alone to counteract the toxicity of cyanide was initially reported in 1895 by Lang. The efficacy of amyl nitrite treatment in cyanide poisoning of the dog model was first reported in 1888 by Pedigo. Further studies in the dog model, which demonstrated the utility of sodium nitrite as a therapeutic intervention, were reported in 1929 by Mladoveanu and Gheorghiu. However, Hugs and Chen et al. independently reported upon the superior efficacy of the combination of sodium nitrite and sodium thiosulfate in 1932-1933. Treatment consisted of intravenously administered 22.5 mg/kg (half the lethal dose) sodium nitrite or 1 g/kg sodium thiosulfate alone or in sequence immediately after subcutaneous injection of sodium cyanide into dogs over a range of doses. Subsequent doses of 10 mg/kg sodium nitrite and/or 0.5 g/kg sodium thiosulfate were administered when clinical signs or symptoms of poisoning persisted or reappeared. Either therapy administered alone increased the dose of sodium cyanide required to cause death, and when administered together, sodium nitrite and sodium thiosulfate resulted in a synergistic effect in raising the lethal dose of sodium cyanide. The combined therapy appeared to have reduced efficacy when therapy was delayed until signs of poisoning (e.g. convulsions) appeared; however, other investigators have reported survival in dogs that were administered antidotal treatment after respiratory arrest had occurred.

Animal studies conducted in other species (e.g., rat, guinea pig, sheep, pigeon and cat) have also supported a synergistic effect of intravenous sodium nitrite and sodium thiosulfate in the treatment of cyanide poisoning.

While intravenous injection of sodium nitrite and sodium thiosulfate was effective in reversing the effects of lethal doses of cyanide in dogs, intramuscular injection of sodium nitrite, with or without sodium thiosulfate, was found not to be effective in the same setting.

16 HOW SUPPLIED/STORAGE AND HANDLING

Each Sodium Thiosulfate carton (NDC 60267-705-50) consists of the following:

- One 50 mL glass vial of sodium thiosulfate injection 250 mg/mL (containing 12.5 grams of sodium thiosulfate);

Storage

Store at controlled room temperature between 20°C and 25°C (68°F to 77°F); excursions permitted from 15 to 30°C (59 to 86°F).

Protect from direct light. Do not freeze.

(Note: Sodium Nitrite must be obtained separately.)

17 PATIENT COUNSELING INFORMATION

Sodium Thiosulfate Injection is indicated for cyanide poisoning and in this setting, patients will likely be unresponsive or may have difficulty in comprehending counseling information.

Hypotension

When feasible, patients should be informed of the possibility of hypotension.

Monitoring

Where feasible, patients should be informed of the need for close monitoring of blood pressure and oxygenation.

Lactation

Advise women that breastfeeding is not recommended during treatment with Sodium Thiosulfate Injection [see Use in Specific Populations (8.2)].

Hope Pharmaceuticals, Scottsdale, Arizona 85260

US PATENTS 8496973, 9345724, and 9585912

PRINCIPAL DISPLAY PANEL - 50 mL Vial Carton

NDC 60267-705-50
Rx Only

Sodium Thiosulfate
Injection, USP

12.5 grams/50 mL
(250 mg/mL)

FOR INTRAVENOUS USE
SINGLE DOSE ONLY

Any unused portion of a vial
should be discarded.

Use with
Sodium Nitrite
for Treatment of
Cyanide Poisoning

Manufactured for:

HOPE
PHARMACEUTICALS ™

Scottsdale, AZ 85260 U.S.A.